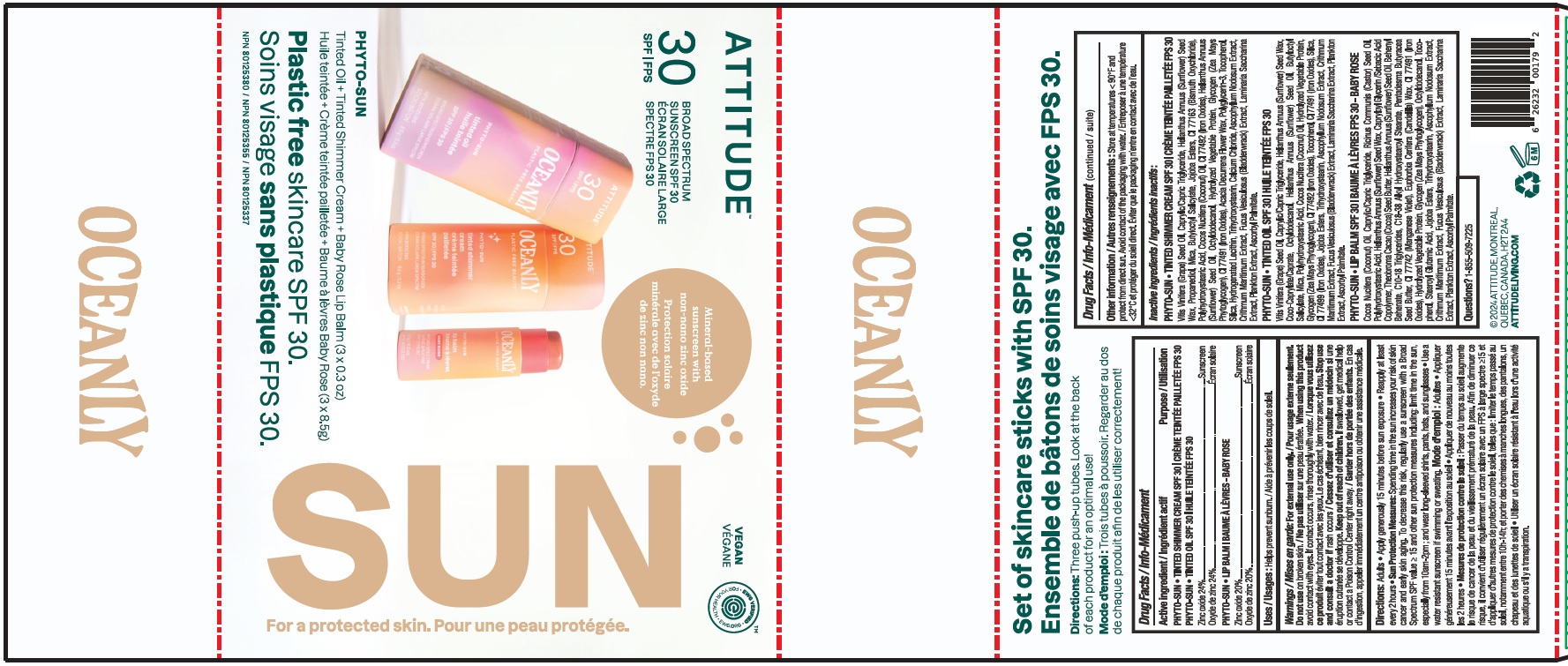 DRUG LABEL: ATTITUDE Oceanly Phyto-Sun Kit SPF 30
NDC: 61649-179 | Form: KIT | Route: TOPICAL
Manufacturer: 9055-7588 Quebec Inc. DBA Attitude
Category: otc | Type: HUMAN OTC DRUG LABEL
Date: 20251020

ACTIVE INGREDIENTS: ZINC OXIDE 24 g/100 g; ZINC OXIDE 24 g/100 g; ZINC OXIDE 20 g/100 g
INACTIVE INGREDIENTS: ASCOPHYLLUM NODOSUM; HELIANTHUS ANNUUS SEED WAX; BUTYLOCTYL SALICYLATE; POLYHYDROXYSTEARIC ACID (2300 MW); .ALPHA.-TOCOPHEROL; MICA; JOJOBA OIL; POLYGLYCERIN-3; SUNFLOWER OIL; MEDIUM-CHAIN TRIGLYCERIDES; FERRIC OXIDE YELLOW; SILICON DIOXIDE; CRITHMUM MARITIMUM; PROPANEDIOL; SACCHARINA LATISSIMA THALLUS; BISMUTH OXYCHLORIDE; COCONUT OIL; HYDROLYZED WHEAT PROTEIN (ENZYMATIC, 3000 MW); CALCIUM CHLORIDE; ACACIA DECURRENS FLOWER WAX; OCTYLDODECANOL; GLYCOGEN; HYDROGENATED SOYBEAN LECITHIN; TRIHYDROXYSTEARIN; FUCUS VESICULOSUS; FERRIC OXIDE RED; ASCORBYL PALMITATE; HYDROLYZED SOY PROTEIN (ENZYMATIC; 2000 MW); CORN; GRAPE SEED OIL; TETRASELMIS SUECICA; TETRASELMIS SUECICA; FERROSOFERRIC OXIDE; BUTYLOCTYL SALICYLATE; JOJOBA OIL; SACCHARINA LATISSIMA; SILICON DIOXIDE; OCTYLDODECANOL; GRAPE SEED OIL; MEDIUM-CHAIN TRIGLYCERIDES; CRITHMUM MARITIMUM; ASCORBYL PALMITATE; CORN; GLYCOGEN; POLYHYDROXYSTEARIC ACID (2300 MW); COCONUT OIL; COCO-CAPRYLATE/CAPRATE; SUNFLOWER OIL; MICA; FERRIC OXIDE YELLOW; ALPHA-TOCOPHEROL; HYDROLYZED WHEAT PROTEIN (ENZYMATIC, 3000 MW); ASCOPHYLLUM NODOSUM; TRIHYDROXYSTEARIN; FERRIC OXIDE RED; FUCUS VESICULOSUS; HELIANTHUS ANNUUS SEED WAX; HYDROLYZED SOY PROTEIN (ENZYMATIC; 2000 MW); COCONUT OIL; TRIHYDROXYSTEARIN; BEHENYL BEHENATE; C18-38 ALKYL HYDROXYSTEAROYL STEARATE; CANDELILLA WAX; SUNFLOWER OIL; MANGANESE VIOLET; HYDROLYZED WHEAT PROTEIN (ENZYMATIC, 3000 MW); .ALPHA.-TOCOPHEROL; MEDIUM-CHAIN TRIGLYCERIDES; POLYHYDROXYSTEARIC ACID (2300 MW); CAPRYLOYL GLYCERIN/SEBACIC ACID COPOLYMER (2000 MPA.S); GLYCOGEN; STEAROYL GLUTAMIC ACID; CORN; HELIANTHUS ANNUUS SEED WAX; ASCOPHYLLUM NODOSUM; FUCUS VESICULOSUS; SACCHARINA LATISSIMA; ASCORBYL PALMITATE; HYDROLYZED SOY PROTEIN (ENZYMATIC; 2000 MW); COCOA BUTTER; JOJOBA OIL; CASTOR OIL; CRITHMUM MARITIMUM; PENTADESMA BUTYRACEA WHOLE; C10-18 TRIGLYCERIDES; OCTYLDODECANOL; FERRIC OXIDE RED; TETRASELMIS SUECICA

ATTITUDE Oceanly Sun Kit SPF 30

ATTITUDE Oceanly Phyto-sun Tinted Shimmer Cream SPF 30

DRUG FACTS

ACTIVE INGREDIENT

Zinc oxide (24 %)

PURPOSE

Sunscreen

INDICATIONS AND USAGE

Helps prevent sunburn.

WARNINGS

For external use only.

When using this product avoid contact with eyes. If contact occurs, rinse thoroughly with water.

Do not use on broken skin.

Keep out of reach of children. If swallowed, get medical help or contact a Poison Control Center right away.

Stop use and consult a doctor if rash occurs.

DOSAGE AND ADMINISTRATION

Adults.

- Apply generously 15 minutes before sun exposure.
- Reapply at least every 2 hours.
- Sun Protection Measures: Spending time in the sun increases your risk of skin cancer and early aging. To decrease this risk, regularly use a sunscreen with a Broad Spectrum SPFvalue of 15 or higher and other sun protection measures including: limit time in the sun, especially from 10am-2pm; and wear long-sleeved shirts, pants, hats and sunglasses.
- Use a water resistant sunscreen if swimming or sweating.

INACTIVE INGREDIENT

Vitis Vinifera (Grape) Seed Oil, Caprylic/Capric Triglyceride, Helianthus Annuus (Sunflower) Seed Wax, Propanediol, Mica, Butyloctyl Salicylate, Jojoba Esters, CI 77163 (Bismuth Oxychloride), Polyhydroxystearic Acid, Cocos Nucifera (Coconut) Oil, CI 77492 (Iron Oxides), Helianthus Annuus (Sunflower) Seed Oil, Octyldodecanol, Hydrolyzed Vegetable Protein, Glycogen (Zea Mays Phytoglycogen), CI 77491 (Iron Oxides), Acacia Decurrens Flower Wax, Polyglycerin-3, Tocopherol, Silica, Hydrogenated Lecithin, Trihydroxystearin, Calcium Chloride, Ascophyllum Nodosum Extract, Crithmum Maritimum Extract, Fucus Vesiculosus (Bladderwrack) Extract, Laminaria Saccharina Extract, Plankton Extract, Ascorbyl Palmitate.

STORAGE AND HANDLING

Store at temperatures < 90F and protect from direct sun. Avoid contact of packaging with water.

Questions ? 1-855-509-7225

ATTITUDE Oceanly Phyto-sun Tinted Oil SPF 30

DRUG FACTS

ACTIVE INGREDIENT

Zinc oxide (24 %)

PURPOSE

Sunscreen

INDICATIONS AND USAGE

Helps prevent sunburn.

WARNINGS

For external use only.

Do not use on broken skin.

When using this product avoid contact with eyes. If contact occurs, rinse thoroughly with water.

Keep out of reach of children. If swallowed, get medical help or contact a Poison Control Center right away.

Stop use and consult a doctor if rash occurs.

DOSAGE AND ADMINISTRATION

Adults.

- Apply generously 15 minutes before sun exposure.
- Reapply at least every 2 hours.
- Sun Protection Measures: Spending time in the sun increases your risk of skin cancer and early aging. To decrease this risk, regularly use a sunscreen with a Broad Spectrum SPFvalue of 15 or higher and other sun protection measures including: limit time in the sun, especially from 10am-2pm; and wear long-sleeved shirts, pants, hats and sunglasses.
- Use a water resistant sunscreen if swimming or sweating.

INACTIVE INGREDIENT

Vitis Vinifera (Grape) Seed Oil, Caprylic/Capric Triglyceride, Helianthus Annuus (Sunflower) Seed Wax, Coco-Caprylate/Caprate, Octyldodecanol, Helianthus Annuus (Sunflower) Seed Oil, Butyloctyl Salicylate, Mica, Polyhydroxystearic Acid, Cocos Nucifera (Coconut) Oil, Hydrolyzed Vegetable Protein, Glycogen (Zea Mays Phytoglycogen), CI 77492 (Iron Oxides), Tocopherol, CI 77491 (Iron Oxides), Silica, CI 77499 (Iron Oxides), Jojoba Esters, Trihydroxystearin, Ascophyllum Nodosum Extract, Crithmum Maritimum Extract, Fucus Vesiculosus (Bladderwrack) Extract, Laminaria Saccharina Extract, Plankton Extract, Ascorbyl Palmitate.

STORAGE AND HANDLING

Store at temperatures < 90F and protect from direct sun. Avoid contact of packaging with water.

Questions ? 1-855-509-7225

ATTITUDE Oceanly Phyto-sun Lip Balm SPF 30 Baby Rose

DRUG FACTS

ACTIVE INGREDIENT

Zinc oxide (20 %)

PURPOSE

Sunscreen

INDICATIONS AND USAGE

Helps prevent sunburn.

WARNINGS

For external use only.

Do not use on broken skin.

Keep out of reach of children. If swallowed, get medical help or contact a Poison Control Center right away.

Stop use and consult a doctor if rash occurs.

DOSAGE AND ADMINISTRATION

Adults.

- Apply generously 15 minutes before sun exposure.
- Reapply at least every 2 hours, after eating or drinking.
- Sun Protection Measures: Spending time in the sun increases your risk of skin cancer and early aging. To decrease this risk, regularly use a sunscreen with a Broad Spectrum SPFvalue of 15 or higher and other sun protection measures including: limit time in the sun, especially from 10am-2pm; and wear long-sleeved shirts, pants, hats and sunglasses.
- Use a water resistant sunscreen if swimming or sweating.

INACTIVE INGREDIENT

Cocos Nucifera (Coconut) Oil, Caprylic/Capric Triglyceride, Ricinus Communis (Castor) Seed Oil, Polyhydroxystearic Acid, Helianthus Annuus (Sunflower) Seed Wax, Capryloyl Glycerin/Sebacic Acid Copolymer, Theobroma Cacao (Cocoa) Seed Butter, Helianthus Annuus (Sunflower) Seed Oil, Behenyl Behenate, C10-18 Triglycerides, C18-38 Alkyl Hydroxystearoyl Stearate, Pentadesma Butyracea Seed Butter, CI 77742 (Manganese Violet), Euphorbia Cerifera (Candelilla) Wax, CI 77491 (Iron Oxides), Hydrolyzed Vegetable Protein, Glycogen (Zea Mays Phytoglycogen), Octyldodecanol, Tocopherol, Stearoyl Glutamic Acid, Jojoba Esters, Trihydroxystearin, Ascophyllum Nodosum Extract, Crithmum Maritimum Extract, Fucus Vesiculosus (Bladderwrack) Extract, Laminaria Saccharina Extract, Plankton Extract, Ascorbyl Palmitate.

STORAGE AND HANDLING

Store at temperatures < 90F and protect from direct sun. Avoid contact of packaging with water.

Questions ? 1-855-509-7225

PACKAGE LABEL

ATTITUDE

Oceanly

SPF 30

Broad spectrum sunscreen SPF 30

Mineral-based sunscreen with non-nano zinc oxide

Vegan

EWG Verified

Phyto-sun

Tinted oil + Tinted shimmer cream + Baby Rose Lip Balm (3 x 0.3 oz)

Plastic free skincare SPF 30

NPN 80125380 / NPN 80125355 / NPN 80125337

SUN For a protected skin